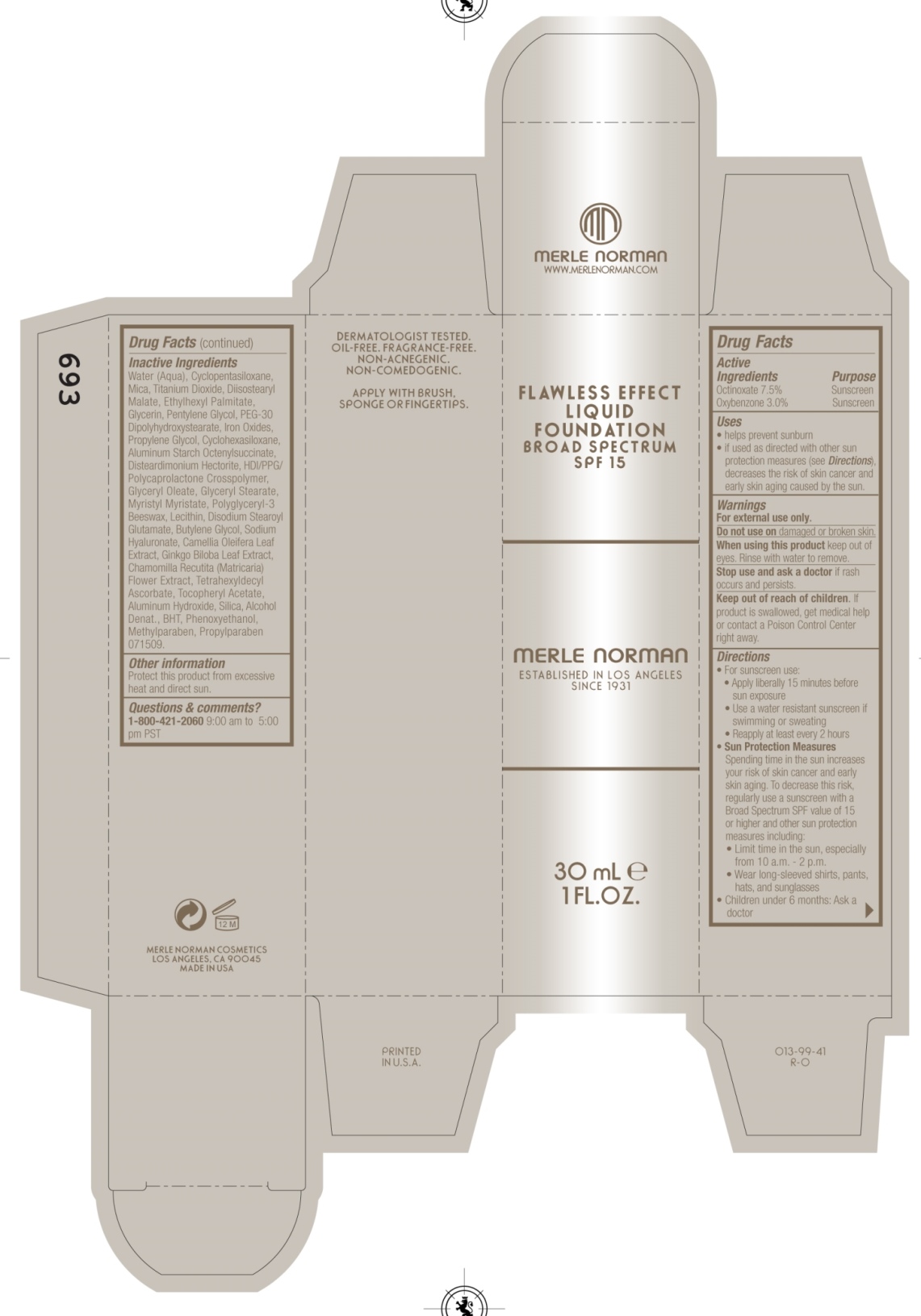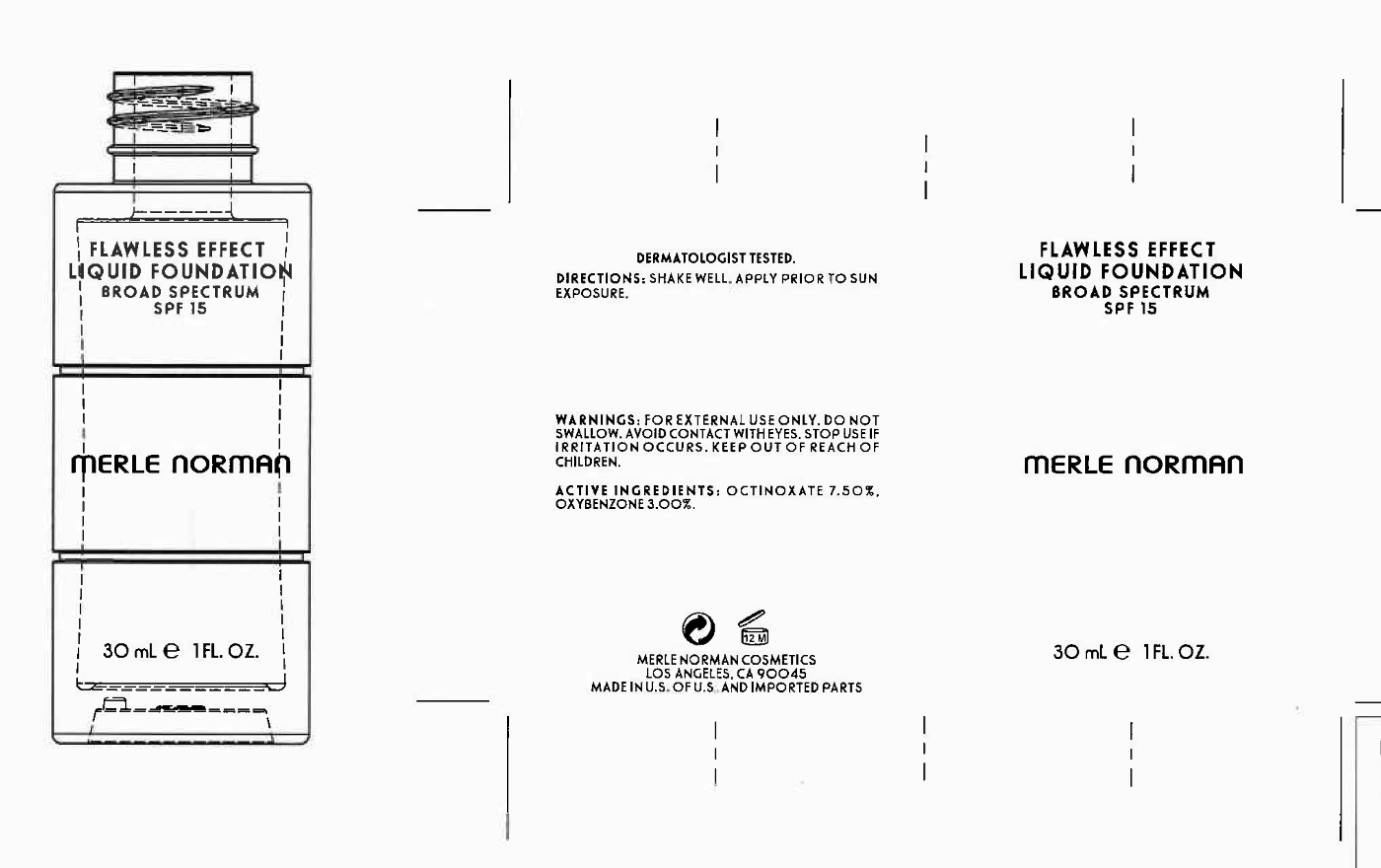 DRUG LABEL: Flawless Effect Liquid Foundation SPF 15
NDC: 57627-113 | Form: LIQUID
Manufacturer: Merle Norman Cosmetics, Inc
Category: otc | Type: HUMAN OTC DRUG LABEL
Date: 20251119

ACTIVE INGREDIENTS: OXYBENZONE 0.9 g/30 g; OCTINOXATE 2.25 g/30 g
INACTIVE INGREDIENTS: CYCLOMETHICONE 5; MICA; TITANIUM DIOXIDE; ETHYLHEXYL PALMITATE; GLYCERIN; PENTYLENE GLYCOL; PEG-30 DIPOLYHYDROXYSTEARATE; FERROUS OXIDE; FERRIC OXIDE RED; FERRIC OXIDE YELLOW; FERROSOFERRIC OXIDE; PROPYLENE GLYCOL; CYCLOMETHICONE 6; ALUMINUM STARCH OCTENYLSUCCINATE; GLYCERYL 1-OLEATE; GLYCERYL MONOSTEARATE; MYRISTYL MYRISTATE; DISODIUM STEAROYL GLUTAMATE; BUTYLENE GLYCOL; HYALURONATE SODIUM; CAMELLIA OLEIFERA LEAF; GINKGO; CHAMOMILE; TETRAHEXYLDECYL ASCORBATE; ALUMINUM HYDROXIDE; SILICON DIOXIDE; BUTYLATED HYDROXYTOLUENE; PHENOXYETHANOL; METHYLPARABEN; PROPYLPARABEN

Merle Norman Flawless Effect Liquid Foundation SPF 15

Active Ingredients

Octinoxate 7.50%

Oxybenzone 3.00%

Uses
· helps prevent sunburn
· If used as directed with other sun protection measures (see Directions),
decreases the risk of skin cancer and early skin aging caused by the sun

Keep out of reach of children. If product is swallowed, get medical help or
contact a Poison Control Center right away

Stop use and ask a doctor if rash occurs

Warnings
· For external use only
· Do not use on damaged or broken skin
· When using this product keep out of eyes. Rinse with water to remove.

Directions
For Sunscreen Use:
· Apply liberally 15 minutes before sun exposure
· Use a water resistant sunscreen if swimming or sweating
· Reapply at least every 2 hours
· Sun Protection Measures. Spending time in the sun increases your risk of skin
cancer and early skin aging. To decrease this risk, regularly use a sunscreen
with broad spectrum SPF of 15 or higher and other sun protection measures
including:
· limit time in the sun, especially from 10 a.m. - 2 p.m.
· wear long-sleeve shirts, pants, hats, and sunglasses
· Children under 6 months: Ask a doctor

INACTIVE INGREDIENT

Water(aqua), cyclopentasiloxane , mica, titanium dioxide, diisostearyl malate, ethylhexyl palmitate, glycerin, pentylene glycol, peg-30 dipolyhydroxystearate, iron oxides, propylene glycol, cyclohexasiloxane, aluminum starch octenylsuccinate, disteardimonium hectorite, hdi/ppg/polycaprolactone crosspolymer, glyceryl oleate, glyceryl stearate, myristyl myristate, polyglyceryl-3 beeswax, lecithin, disodium stearoyl glutamate, Butylene Glycol, sodium hyaluronate, camellia oleifera leaf extract, ginkgo biloba leaf extract, chamomilla recutita (matricaria) flower extract, tetrahexyldecyl ascorbate, tocopheryl acetate, aluminum hydroxide (Cl 77002), silica, alcohol denat., BHT, phenoxyethanol, methylparaben, propylparaben

PACKAGE LABEL

Flawless Effect Liquid Foundation SPF 15

Merle Norman

30 mL 1 FL. OZ.